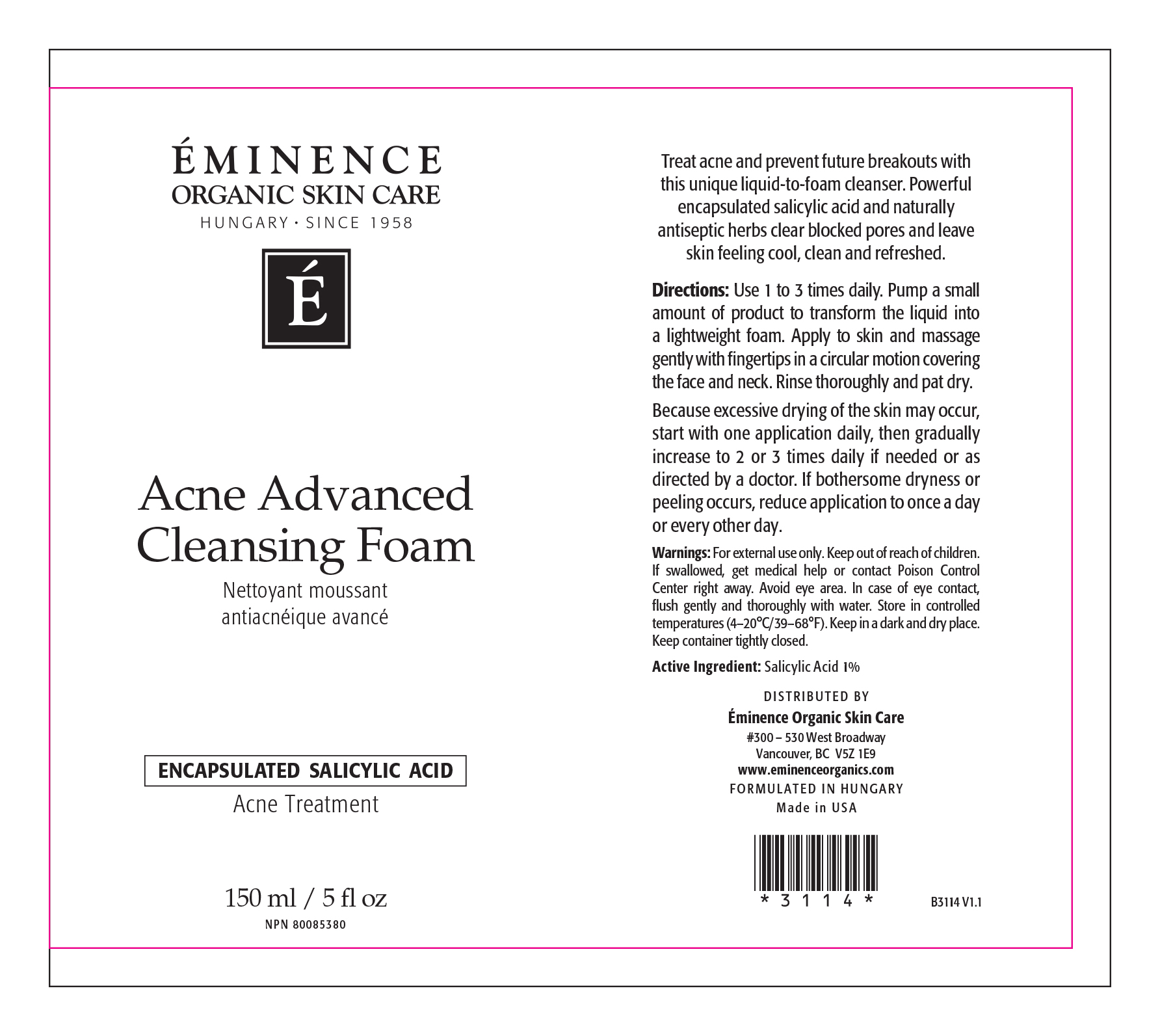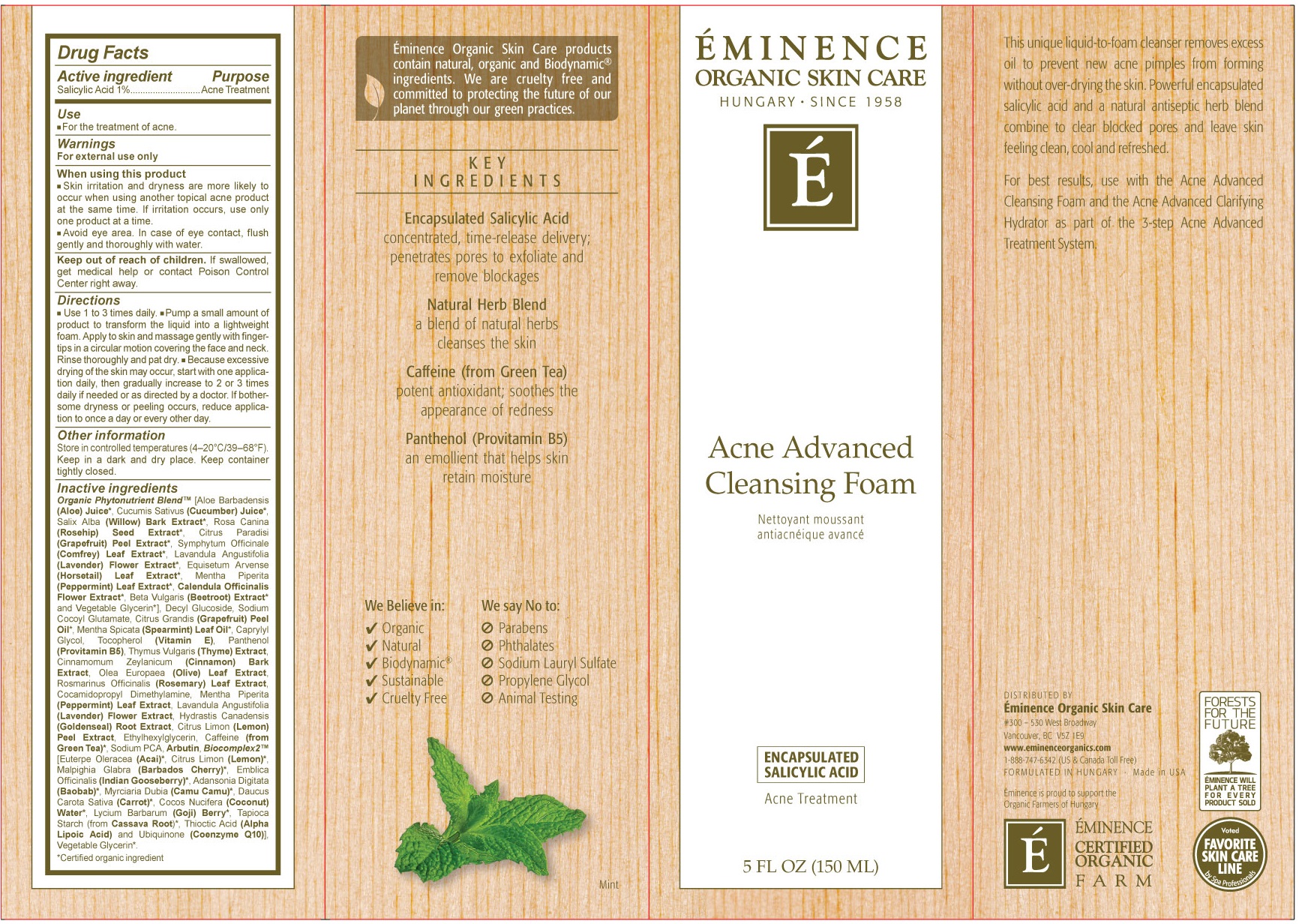 DRUG LABEL: Acne Advanced Cleansing
NDC: 15751-3010 | Form: LIQUID
Manufacturer: Eminence Organic Skin Care Ltd.
Category: otc | Type: HUMAN OTC DRUG LABEL
Date: 20181114

ACTIVE INGREDIENTS: SALICYLIC ACID 10 mg/1 mL
INACTIVE INGREDIENTS: ALOE; CUCUMBER; ROSA MOSCHATA OIL; GRAPEFRUIT; SYMPHYTUM UPLANDICUM LEAF; PEPPERMINT; CALENDULA OFFICINALIS FLOWER; BETA VULGARIS; GLYCERIN; DECYL GLUCOSIDE; SODIUM COCOYL GLUTAMATE; SPEARMINT; CAPRYLYL GLYCOL; TOCOPHEROL; DEXPANTHENOL; THYME; CINNAMON; OLIVE OIL; ROSEMARY; COCAMIDOPROPYL DIMETHYLAMINE; GOLDENSEAL; LEMON; ETHYLHEXYLGLYCERIN; GREEN TEA LEAF; SODIUM PYRROLIDONE CARBOXYLATE; ARBUTIN; ACAI; CARROT; COCONUT; STARCH, TAPIOCA; THIOCTIC ACID; UBIDECARENONE

Acne Advanced Cleansing Foam

Active ingredient

Salicylic Acid 1%

Purpose

Acne Treatment

Use

- For the treatment of acne.

Warnings

For external use only

When using this product

- Skin irritation and dryness are more likely to occur when using another topical acne product at the same time. If irritation occurs, use only one product at a time.
- Avoid eye area. In case of eye contact, flush gently and thoroughly with water.

Keep out of reach of children.

If swallowed, get medical help or contact Poison Control Center right away.

Direcitons

- Use 1 to 3 times daily.
- Pump a small amount of product to transform the liquid into a lightweight foam. Apply to skin and massage gently with fingertips in a circular motion covering the face and neck. Rinse thoroughly and pat dry.
- Because excessive drying of the skin may occur, strar with one application daily, then gradually increase to 2 ot 3 times daily if needed or as directed by a doctor. if bothersome dryness or peeling occurs, reduce application to once a day or every other day.

Other information

Store in controlled temperatures (4-20°C/39-68°F). Keep in a dark and dry place. Keep container tightly closed.

Inactive ingredients

Organic Phytonutrient Blend (Aloe Barbadensis (Aloe) Juice, Cucumis Sativus (Cucumber) Juice, Salix Alba (Willow) Bark Extract, Rosa Canina (Rosehip) Seed Extract, Citrus Paradisi (Grapefruit) Peel Extract, Symphytum Officinale (Comfrey) Leaf Extract, Lavandula Angustifolia (Lavender) Flower Extract, Equisetum Argense (Horsetail Leaf Extract, Mentha Piperita (Peppermint) Leaf Extract, Calendula Officinalis Flower Extract, Beta Vulgaris (Beetroot) Extract and Vegetable Glyceri], Decyl Glucoside, Sodium Cocoyl Glutamate, Citrus Grandis (Grapefruit) Peel Oil, Metha Spicata (Spearmint) Leaf Oil, Caprylyl Glycol, Tocopherol (Vitamin E), Panthenol (Provitamin B5), Thymus Vulgans (Thyme) Extract, Cinnamomum Zeylanicum (Cinnamon) Bark Extract, Ole Europaea (Olive) Leaf Extract, Rosmarinus Officinalis (Rosemary) Leaf Extract, Cocamidopropyl Dimethylamine, Mentha Piperita (Peppermint) Leaf Extract, Lavandula Angustifolia (Lavender) Flower Extract, Hydrastis Canadensis (Goldenseal) Root Extract, Citrus Limon (Lemon) Peel Extract, Ethylhexylglycerin, Caffeine (from Green Tea), Sodium PCA, Arbutin, Biocomplex2 [Euterpe Oleracea (Acai), Citrus Limon (Lemon), Malpighia Glabra (Barbados Cherry), Emblica Officinalis (Indian Gooseberry), Adansonia Digitata (Baobab), Myrciaria Dubia (Camu Camu), Daucus Carota Sativa (Carrot), Cocos Nucifera (Coconut) Water, Lycium Barbarum (Goji) Berry, Tapioca Starch (from Cassave Root), Thioctic Acid (Alpha Lipoic Acid) and Ubiquinone (Coenzyme Q10), Vegetable Glycerin.
*Certified organic ingredient